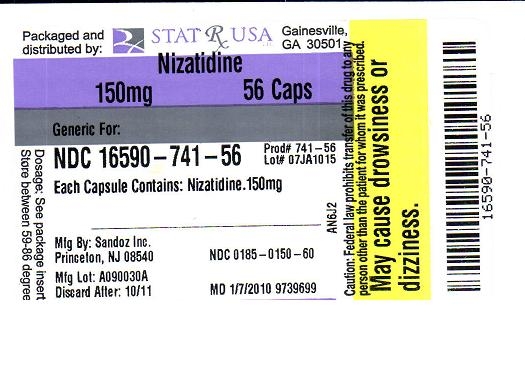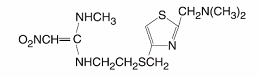 DRUG LABEL: Nizatidine
NDC: 16590-741 | Form: CAPSULE
Manufacturer: nizatidine
Category: prescription | Type: HUMAN PRESCRIPTION DRUG LABEL
Date: 20100114

ACTIVE INGREDIENTS: Nizatidine 150 mg/1 1

Nizatidine Insert & Label

DESCRIPTION

Nizatidine USP is a histamine H2-receptor antagonist. Chemically, it is N-[2-[[[2-[(dimethylamino)methyl]-4-thiazolyl]methyl]thio]ethyl]-N’-methyl-2-nitro-1,1-ethenediamine.

The structural formula is as follows:

Nizatidine has the molecular formula C12H21N5O2S2 representing a molecular weight of 331.46. It is an off-white to buff crystalline solid that is soluble in water. Nizatidine has a bitter taste and mild sulfur-like odor.

Each capsule for oral administration contains nizatidine 150 mg (0.45 mmol) or 300 mg (0.91 mmol), pregelatinized starch, povidone, corn starch, talc, croscarmellose sodium, dimethicone, gelatin, titanium dioxide, pharmaceutical glaze (modified), synthetic black iron oxide, propylene glycol, FD and C blue #2 aluminum lake, FD and C red #40 aluminum lake, FD and C blue #1 aluminum lake, and D and C yellow #10 aluminum lake. The 150 mg capsule also contains yellow iron oxide, and the 300 mg capsule also contains D and C red #28, FD and C blue #1, and FD and C yellow #6.

CLINICAL PHARMACOLOGY

Nizatidine is a competitive, reversible inhibitor of histamine at the histamine H2-receptors, particularly those in the gastric parietal cells.

Antisecretory Activity Effects on Acid Secretion

Nizatidine significantly inhibited nocturnal gastric acid secretion for up to 12 hours. Nizatidine also significantly inhibited gastric acid secretion stimulated by food, caffeine, betazole, and pentagastrin .

INDICATIONS AND USAGE

Nizatidine is indicated for up to 8 weeks for the treatment of active duodenal ulcer. In most patients, the ulcer will heal within 4 weeks.

Nizatidine is indicated for maintenance therapy for duodenal ulcer patients, at a reduced dosage of 150 mg h.s. after healing of an active duodenal ulcer. The consequences of continuous therapy with nizatidine for longer than 1 year are not known.

Nizatidine is indicated for up to 12 weeks for the treatment of endoscopically diagnosed esophagitis, including erosive and ulcerative esophagitis, and associated heartburn due to GERD.

Nizatidine is indicated for up to 8 weeks for the treatment of active benign gastric ulcer. Before initiating therapy, care should be taken to exclude the possibility of malignant gastric ulceration.

CONTRAINDICATIONS

Nizatidine is contraindicated in patients with known hypersensitivity to the drug. Because cross sensitivity in this class of compounds has been observed, H2-receptor antagonists, including nizatidine, should not be administered to patients with a history of hypersensitivity to other H2-receptor antagonists.

PRECAUTIONS

PRECAUTIONSGeneral

Symptomatic response to nizatidine therapy does not preclude the presence of gastric malignancy.

Because nizatidine is excreted primarily by the kidney, dosage should be reduced in patients with moderate to severe renal insufficiency (see DOSAGE AND ADMINISTRATION).

Pharmacokinetic studies in patients with hepatorenal syndrome have not been done. Part of the dose of nizatidine is metabolized in the liver. In patients with normal renal function and uncomplicated hepatic dysfunction, the disposition of nizatidine is similar to that in normal subjects.

Laboratory Tests

False-positive tests for urobilinogen with Multistix® may occur during therapy with nizatidine.

Drug Interactions

No interactions have been observed between nizatidine and theophylline, chlordiazepoxide, lorazepam, lidocaine, phenytoin, and warfarin. Nizatidine does not inhibit the cytochrome P-450-linked drug-metabolizing enzyme system; therefore, drug interactions mediated by inhibition of hepatic metabolism are not expected to occur. In patients given very high doses (3,900 mg) of aspirin daily, increases in serum salicylate levels were seen when nizatidine, 150 mg b.i.d., was administered concurrently.

Carcinogenesis, Mutagenesis, Impairment of Fertility

A 2-year oral carcinogenicity study in rats with doses as high as 500 mg/kg/day (about 13 times the recommended human dose based on body surface area) showed no evidence of a carcinogenic effect. There was a dose-related increase in the density of enterochromaffin-like (ECL) cells in the gastric oxyntic mucosa. In a 2-year study in mice, there was no evidence of a carcinogenic effect in male mice; although hyperplastic nodules of the liver were increased in the high-dose males as compared with placebo. Female mice given the high dose of nizatidine (2,000 mg/kg/day, about 27 times the recommended human dose based on body surface area) showed marginally statistically significant increases in hepatic carcinoma and hepatic nodular hyperplasia with no numerical increase seen in any of the other dose groups. The rate of hepatic carcinoma in the high-dose animals was within the historical control limits seen for the strain of mice used. The female mice were given a dose larger than the maximum tolerated dose, as indicated by excessive (30%) weight decrement as compared with concurrent controls and evidence of mild liver injury (transaminase elevations). The occurrence of a marginal finding at high dose only in animals given an excessive and somewhat hepatotoxic dose, with no evidence of a carcinogenic effect in rats, male mice, and female mice (given up to 360 mg/kg/day, about 5 times the recommended human dose based on body surface aea), and a negative mutagenicity battery are not considered evidence of a carcinogenic potential for nizatidine.

Nizatidine was not mutagenic in a battery of tests performed to evaluate its potential genetic toxicity, including bacterial mutation tests, unscheduled DNA synthesis, sister chromatid exchange, mouse lymphoma assay, chromosome aberration tests, and a micronucleus test.

In a 2-generation, perinatal and postnatal fertility study in rats, doses of nizatidine up to 650 mg/kg/day (about 17.5 times the recommended human dose based on body surface area) produced no adverse effects on the reproductive performance of parental animals or their progeny.

Pregnancy

Teratogenic Effects–Pregnancy Category B: Oral reproduction studies in pregnant rats at doses up to 1500 mg/kg/day (about 40.5 times the recommended human dose based on body surface area) and in pregnant rabbits at doses up to 275 mg/kg/day (about 14.6 times the recommended human dose based on body surface area) have revealed no evidence of impaired fertility or harm to the fetus due to nizatidine. There are, however, no adequate and well-controlled studies in pregnant women. Because animal reproduction studies are not always predictive of human response, this drug should be used during pregnancy only if clearly needed.

Nursing Mothers

Studies conducted in lactating women have shown that 0.1% of the administered oral dose of nizatidine is secreted in human milk in proportion to plasma concentrations. Because of the growth depression in pups reared by lactating rats treated with nizatidine, a decision should be made whether to discontinue nursing or discontinue the drug, taking into account the importance of the drug to the mother.

Pediatric Use

Safety and effectiveness in pediatric patients have not been established.

Geriatric Use

Of the 955 patients in clinical studies who were treated with nizatidine, 337 (35.3%) were 65 and older. No overall differences in safety or effectiveness were observed between these and younger subjects. Other reported clinical experience has not identified differences in responses between the elderly and younger patients, but greater sensitivity of some older individuals cannot be ruled out.

This drug is known to be substantially excreted by the kidney, and the risk of toxic reactions to this drug may be greater in patients with impaired renal function. Because elderly patients are more likely to have decreased renal function, care should be taken in dose selection, and it may be useful to monitor renal function (see DOSAGE AND ADMINISTRATION).

ADVERSE REACTIONS

Worldwide, controlled clinical trials of nizatidine included over 6,000 patients given nizatidine in studies of varying durations. Placebo-controlled trials in the United States and Canada included over 2,600 patients given nizatidine and over 1,700 given placebo. Among the adverse events in these placebo-controlled trials, anemia (0.2% vs 0%) and urticaria (0.5% vs 0.1%) were significantly more common in the nizatidine group.

Incidence in Placebo-Controlled Clinical Trials in the United States and Canada

Table 5 lists adverse events that occurred at a frequency of 1% or more among nizatidine-treated patients who participated in placebo-controlled trials. The cited figures provide some basis for estimating the relative contribution of drug and nondrug factors to the side effect incidence rate in the population studied.

A variety of less common events were also reported; it was not possible to determine whether these were caused by nizatidine.

Hepatic: Hepatocellular injury, evidenced by elevated liver enzyme tests (SGOT [AST], SGPT [ALT], or alkaline phosphatase), occurred in some patients and was possibly or probably related to nizatidine. In some cases there was marked elevation of SGOT, SGPT enzymes (greater than 500 IU/L) and, in a single instance, SGPT was greater than 2,000 IU/L. The overall rate of occurrences of elevated liver enzymes and elevations to 3 times the upper limit of normal, however, did not significantly differ from the rate of liver enzyme abnormalities in placebo-treated patients. All abnormalities were reversible after discontinuation of nizatidine. Since market introduction, hepatitis and jaundice have been reported. Rare cases of cholestatic or mixed hepatocellular and cholestatic injury with jaundice have been reported with reversal of the abnormalities after discontinuation of nizatidine.

Cardiovascular: In clinical pharmacology studies, short episodes of asymptomatic ventricular tachycardia occurred in 2 individuals administered nizatidine and in 3 untreated subjects.

CNS: Rare cases of reversible mental confusion have been reported.

Endocrine: Clinical pharmacology studies and controlled clinical trials showed no evidence of antiandrogenic activity due to nizatidine. Impotence and decreased libido were reported with similar frequency by patients who received nizatidine and by those given placebo. Rare reports of gynecomastia occurred.

Hematologic: Anemia was reported significantly more frequently in nizatidine- than in placebo-treated patients. Fatal thrombocytopenia was reported in a patient who was treated with nizatidine and another H2-receptor antagonist. On previous occasions, this patient had experienced thrombocytopenia while taking other drugs. Rare cases of thrombocytopenic purpura have been reported.

Integumental: Sweating and urticaria were reported significantly more frequently in nizatidine- than in placebo-treated patients. Rash and exfoliative dermatitis were also reported. Vasculitis has been reported rarely.

Hypersensitivity: As with other H2-receptor antagonists, rare cases of anaphylaxis following administration of nizatidine have been reported. Rare episodes of hypersensitivity reactions (e.g., bronchospasm, laryngeal edema, rash, and eosinophilia) have been reported.

Body as a Whole: Serum sickness-like reactions have occurred rarely in conjunction with nizatidine use.

Genitourinary: Reports of impotence have occurred.

Other: Hyperuricemia unassociated with gout or nephrolithiasis was reported. Eosinophilia, fever, and nausea related to nizatidine administration have been reported.

DOSAGE AND ADMINISTRATIONActive Duodenal Ulcer

The recommended oral dosage for adults is 300 mg once daily at bedtime. An alternative dosage regimen is 150 mg twice daily.

Maintenance of Healed Duodenal Ulcer

The recommended oral dosage for adults is 150 mg once daily at bedtime.

Gastroesophageal Reflux Disease

The recommended oral dosage in adults for the treatment of erosions, ulcerations, and associated heartburn is 150 mg twice daily.

Active Benign Gastric Ulcer

The recommended oral dosage is 300 mg given either as 150 mg twice daily or 300 mg once daily at bedtime. Prior to treatment, care should be taken to exclude the possibility of malignant gastric ulceration.

Dosage Adjustment for Patients With Moderate to Severe Renal Insufficiency

The dose for patients with renal dysfunction should be reduced as follows:

Some elderly patients may have creatinine clearances of less than 50 mL/min, and, based on pharmacokinetic data in patients with renal impairment, the dose for such patients should be reduced accordingly. The clinical effects of this dosage reduction in patients with renal failure have not been evaluated.

HOW SUPPLIED

Nizatidine Capsules USP, 150 mg are available as white opaque body and yellow opaque cap, imprinted “ 150” on the body and cap in black ink. They are available in bottles of 60 and 500.

Nizatidine Capsules USP, 300 mg are available as white opaque body and peach opaque cap, imprinted “ 300” on the body and cap in black ink. They are available in bottles of 30 and 100.

Store at 20°-25°C (68°-77°F) [see USP Controlled Room Temperature].

Sandoz, Inc.

Princeton, NJ 08540

PACKAGE LABEL

Lable Image